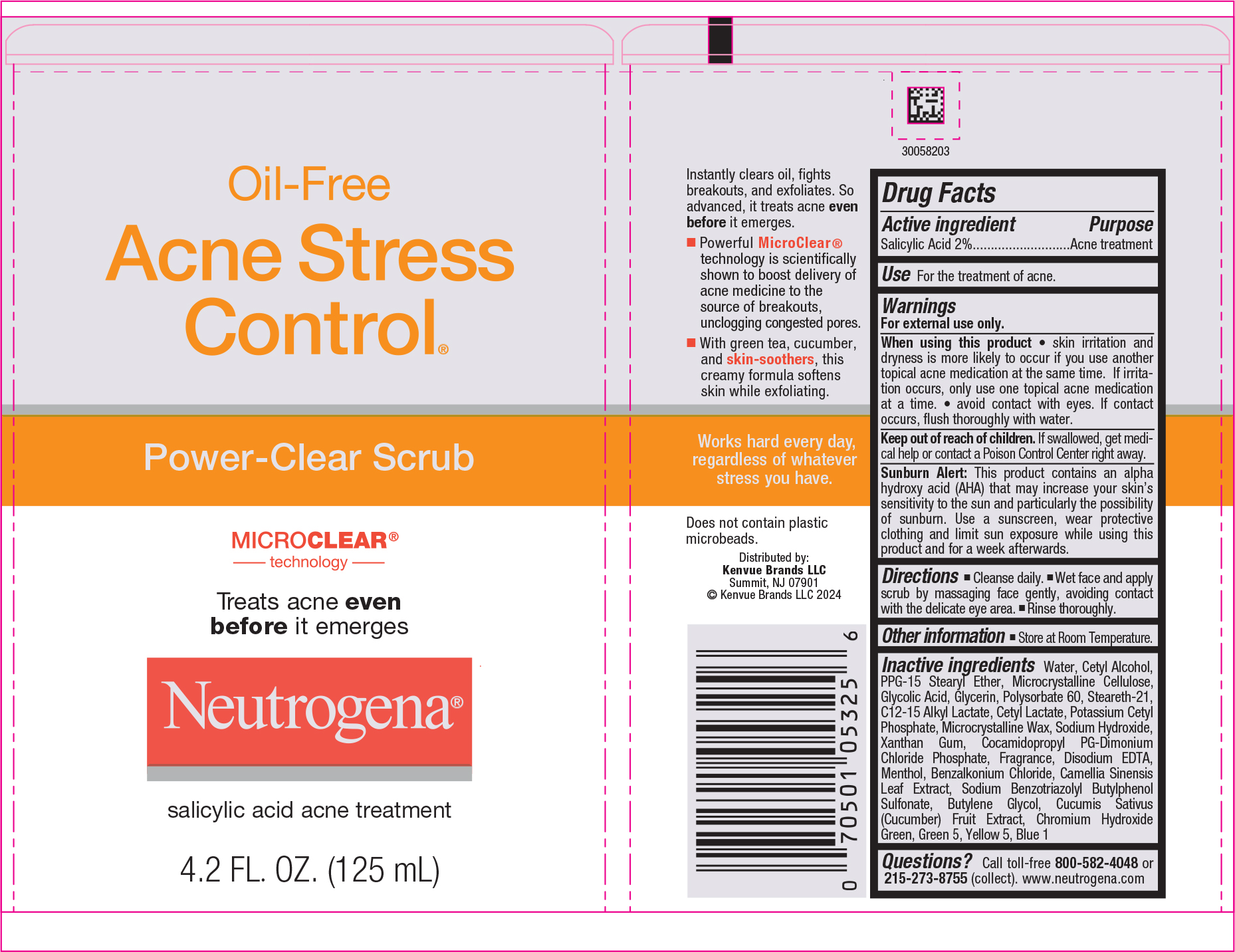 DRUG LABEL: Neutrogena Oil Free Acne Stress Control Power Clear Scrub
NDC: 69968-0073 | Form: GEL
Manufacturer: Kenvue Brands LLC
Category: otc | Type: HUMAN OTC DRUG LABEL
Date: 20241211

ACTIVE INGREDIENTS: SALICYLIC ACID 20 mg/1 mL
INACTIVE INGREDIENTS: WATER; CETYL ALCOHOL; PPG-15 STEARYL ETHER; MICROCRYSTALLINE CELLULOSE; GLYCOLIC ACID; GLYCERIN; STEARETH-21; POLYSORBATE 60; C12-15 ALKYL LACTATE; CETYL LACTATE; POTASSIUM CETYL PHOSPHATE; SODIUM HYDROXIDE; MICROCRYSTALLINE WAX; XANTHAN GUM; COCAMIDOPROPYL PROPYLENE GLYCOL-DIMONIUM CHLORIDE PHOSPHATE; EDETATE DISODIUM ANHYDROUS; MENTHOL, UNSPECIFIED FORM; BENZALKONIUM CHLORIDE; SODIUM BENZOTRIAZOLYL BUTYLPHENOL SULFONATE; BUTYLENE GLYCOL; GREEN TEA LEAF; CUCUMBER; CHROMIUM HYDROXIDE GREEN; D&C GREEN NO. 5; FD&C YELLOW NO. 5; FD&C BLUE NO. 1

Neutrogena® Oil-Free Acne Stress Control® Power-Clear Scrub

Drug Facts

Active ingredient

Salicylic Acid 2%

Purpose

Acne treatment

Use

For the treatment of acne.

Warnings

For external use only.

When using this product

- skin irritation and dryness is more likely to occur if you use another topical acne medication at the same time. If irritation occurs, only use one topical acne medication at a time.
- avoid contact with eyes. If contact occurs, flush thoroughly with water.

Keep out of reach of children. If swallowed, get medical help or contact a Poison Control Center right away.

Sunburn Alert

This product contains an alpha hydroxy acid (AHA) that may increase your skin's sensitivity to the sun and particularly the possibility of sunburn. Use a sunscreen, wear protective clothing and limit sun exposure while using this product and for a week afterwards.

Directions

- Cleanse daily.
- Wet face and apply scrub by massaging face gently, avoiding contact with the delicate eye area.
- Rinse thoroughly .

Other information

- Store at Room Temperature.

Inactive ingredients

Water, Cetyl Alcohol, PPG-15 Stearyl Ether, Microcrystalline Cellulose, Glycolic Acid, Glycerin, Polysorbate 60, Steareth-21, C12-15 Alkyl Lactate, Cetyl Lactate, Potassium Cetyl Phosphate, Microcrystalline Wax, Sodium Hydroxide, Xanthan Gum, Cocamidopropyl PG-Dimonium Chloride Phosphate, Fragrance, Disodium EDTA, Menthol, Benzalkonium Chloride, Camellia Sinensis Leaf Extract, Sodium Benzotriazolyl Butylphenol Sulfonate, Butylene Glycol, Cucumis Sativus (Cucumber) Fruit Extract, Chromium Hydroxide Green, Green 5, Yellow 5, Blue 1

Questions?

Call toll-free 800-582-4048 or 215-273-8755 (collect). www.neutrogena.com

Distributed by:
Kenvue Brands LLC
Summit, NJ 07901

PRINCIPAL DISPLAY PANEL - 125 mL Tube Label

Oil-Free
Acne Stress
Control®

Power-Clear Scrub

MICRO CLEAR®
technology

Treats acne even
before it emerges

Neutrogena®

salicylic acid acne treatment

4.2 FL. OZ. (125 mL)